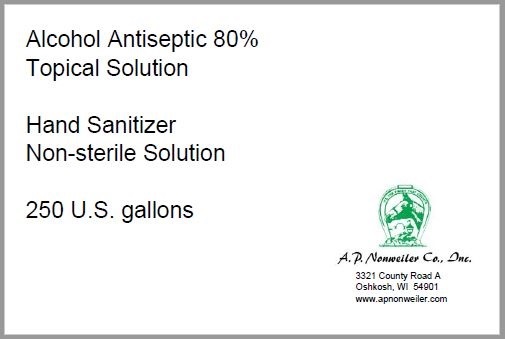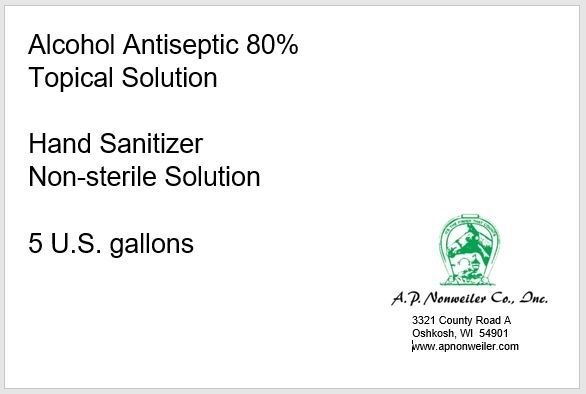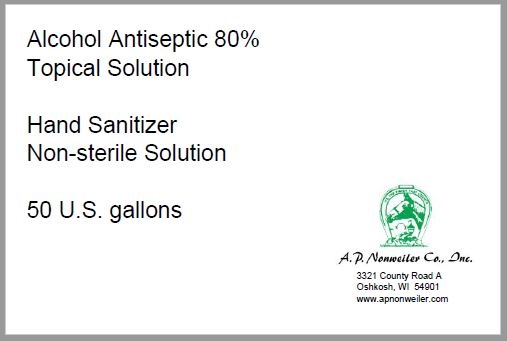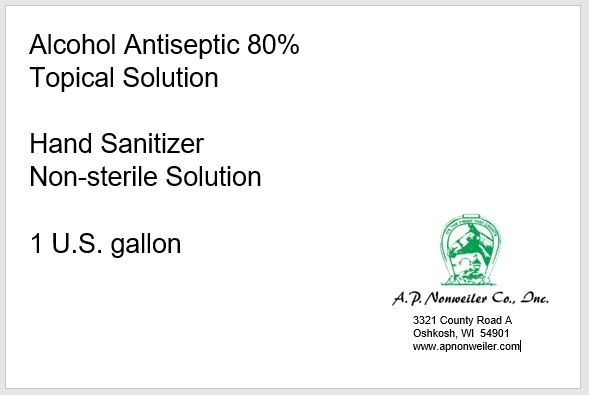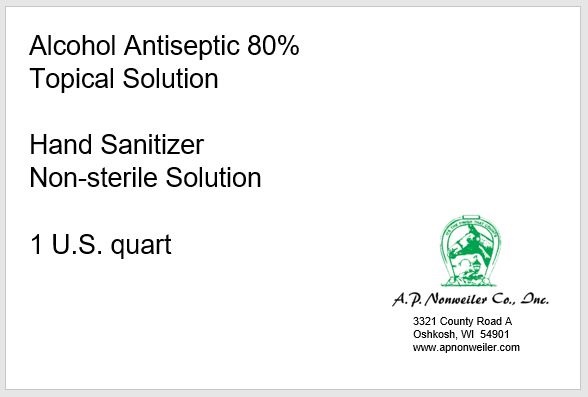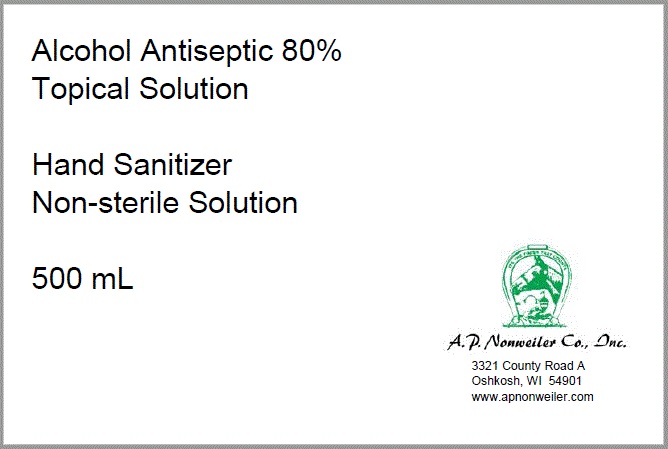 DRUG LABEL: Lewcizer 4
NDC: 74829-361 | Form: LIQUID
Manufacturer: A.P. Nonweiler Co., Inc.
Category: otc | Type: HUMAN OTC DRUG LABEL
Date: 20201028

ACTIVE INGREDIENTS: ALCOHOL 80.8 mL/100 mL
INACTIVE INGREDIENTS: ISOPROPYL ALCOHOL 4.2 mL/100 mL; HYDROGEN PEROXIDE 0.3 mL/100 mL; WATER; GLYCERIN 1.5 mL/100 mL

This is a hand sanitizer manufactured according to the Temporary Policy for Preparation of Certain Alcohol-Based Hand Sanitizer Products During the Public Health Emergency (CoViD-19); Guidance for Industry.

Active Ingredient(s)

Alcohol 80% v/v. Purpose: Antiseptic

Purpose

Antiseptic, Hand Sanitizer

Use

Hand Sanitizer to help reduce bacteria that potentially can cause disease. For use when soap and water are not available.

Warnings

For external use only. Flammable. Keep away from heat or flame

Do not use

- in children less than 2 months of age
- on open skin wounds

When using this product keep out of eyes, ears, and mouth. In case of contact with eyes, rinse eyes thoroughly with water.
Stop use and ask a doctor if irritation or rash occurs. These may be signs of a serious condition.
Keep out of reach of children. If swallowed, get medical help or contact a Poison Control Center right away.

Stop use and ask a doctor if irritation or rash occurs. These may be signs of a serious condition.

Keep out of reach of children. If swallowed, get medical help or contact a Poison Control Center right away.

Directions

- Place enough product on hands to cover all surfaces. Rub hands together until dry.
- Supervise children under 6 years of age when using this product to avoid swallowing.

Other information

- Store between 15-30C (59-86F)
- Avoid freezing and excessive heat above 40C (104F)

Inactive ingredients

HYDROGEN PEROXIDE, GLYCERIN, STERILE WATER

Package Label - Principal Display Panel

500 mL NDC: 74829-361-08

3785.41 mL NDC: 74829-361-01

18927.06 mL NDC: 74829-361-05

189270.59 mL NDC: 74829-361-50

946352.95 mL NDC: 74829-361-25

946.35 mL NDC: 74829-361-04